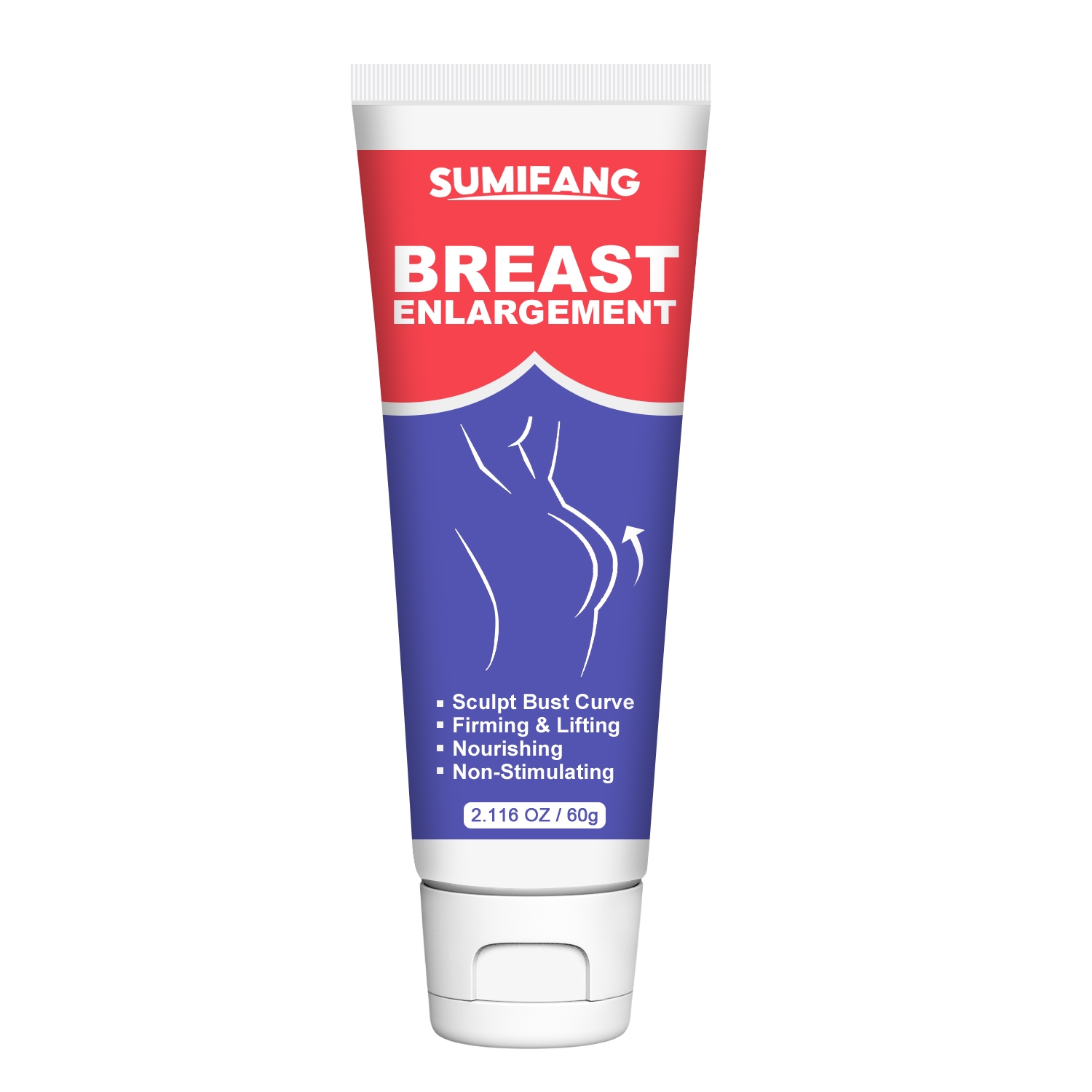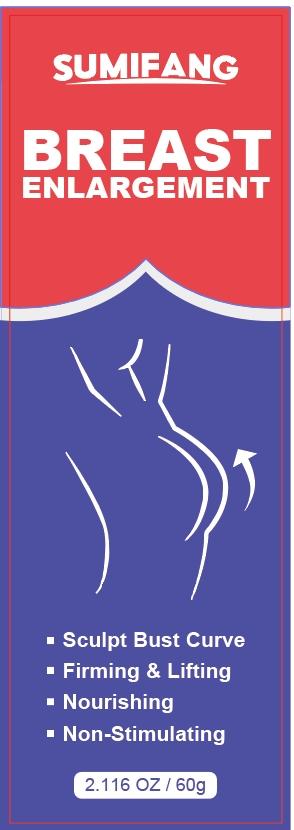 DRUG LABEL: breast massage cream
NDC: 84025-122 | Form: CREAM
Manufacturer: Guangzhou Yanxi Biotechnology Co.. Ltd
Category: otc | Type: HUMAN OTC DRUG LABEL
Date: 20240807

ACTIVE INGREDIENTS: GLYCERIN 5 mg/60 g; PROPANEDIOL 3 mg/60 g
INACTIVE INGREDIENTS: WATER

DOSAGE AND ADMINISTRATION

Cream for massaging and moisturizing the breasts

WARNINGS

Keep out of children

INACTIVE INGREDIENT

Aqua

INDICATIONS AND USAGE

For daily maintenance and care of breast skin

Keep out of children

PURPOSE

Shapes the breasts and firms the breast skin